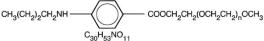 DRUG LABEL: Unknown
Manufacturer: ETHEX Corporation
Category: prescription | Type: HUMAN PRESCRIPTION DRUG LABELING
Date: 20081230

Benzonatate Capsules, USP
100 mg and 200 mg

Rx Only

P5519-1 01/08

DESCRIPTION

Benzonatate, a non-narcotic oral antitussive agent, is 2, 5, 8, 11, 14, 17, 20, 23, 26-nonaoxaoctacosan-28-yl p-(butylamino) benzoate; with a molecular weight of 603.7.

Each benzonatate capsule contains benzonatate, USP, 100 mg or 200 mg.

Benzonatate capsules, USP also contain gelatin, glycerin, methyl/propyl paraben blend, purified water, and titanium dioxide.

CLINICAL PHARMACOLOGY

Benzonatate acts peripherally by anesthetizing the stretch receptors located in the respiratory passages, lungs, and pleura by dampening their activity and thereby reducing the cough reflex at its source. It begins to act within 15 to 20 minutes and its effect lasts for 3 to 8 hours. Benzonatate has no inhibitory effect on the respiratory center in recommended dosage.

INDICATIONS AND USAGE

Benzonatate capsules, USP are indicated for the symptomatic relief of cough.

CONTRAINDICATIONS

Hypersensitivity to benzonatate or related compounds.

WARNINGS

Severe hypersensitivity reactions (including bronchospasm, laryngospasm and cardiovascular collapse) have been reported which are possibly related to local anesthesia from sucking or chewing the capsule instead of swallowing it. Severe reactions have required intervention with vasopressor agents and supportive measures.

Isolated instances of bizarre behavior, including mental confusion and visual hallucinations, have also been reported in patients taking benzonatate capsules, USP in combination with other prescribed drugs.

PRECAUTIONS

Benzonatate is chemically related to anesthetic agents of the para-amino-benzoic acid class (e.g., procaine; tetracaine) and has been associated with adverse CNS effects possibly related to a prior sensitivity to related agents or interaction with concomitant medication.

Information for Patients

Release of benzonatate from the capsule in the mouth can produce a temporary local anesthesia of the oral mucosa and choking could occur. Therefore, the capsules should be swallowed without chewing.

Usage in Pregnancy – Pregnancy Category C

Animal reproduction studies have not been conducted with benzonatate capsules, USP. It is also not known whether benzonatate capsules, USP can cause fetal harm when administered to a pregnant woman or can affect reproduction capacity. Benzonatate capsules, USP should be given to a pregnant woman only if clearly needed.

Nursing Mothers

It is not known whether this drug is excreted in human milk. Because many drugs are excreted in human milk, caution should be exercised when benzonatate capsules, USP are administered to a nursing woman.

Carcinogenesis, Mutagenesis, Impairment of Fertility

Carcinogenicity, mutagenicity, and reproduction studies have not been conducted with benzonatate capsules, USP.

Pediatric Use

Safety and effectiveness in children below the age of 10 have not been established.

ADVERSE REACTIONS

Potential adverse reactions to benzonatate capsules, USP may include:

Hypersensitivity reactions including bronchospasm, laryngospasm, cardiovascular collapse possibly related to local anesthesia from chewing or sucking the capsule.

CNS: sedation; headache; dizziness; mental confusion; visual hallucinations.

GI: constipation, nausea, GI upset.

Dermatologic: pruritus; skin eruptions.

Other: nasal congestion; sensation of burning in the eyes; vague “chilly” sensation; numbness of the chest; hypersensitivity.

Rare instances of deliberate or accidental overdose have resulted in death.

OVERDOSAGE

Overdose may result in death.

The drug is chemically related to tetracaine and other topical anesthetics and shares various aspects of their pharmacology and toxicology. Drugs of this type are generally well absorbed after ingestion.

Signs and Symptoms

If capsules are chewed or dissolved in the mouth, oropharyngeal anesthesia will develop rapidly. CNS stimulation may cause restlessness and tremors which may proceed to clonic convulsions followed by profound CNS depression.

Treatment

Evacuate gastric contents and administer copious amounts of activated charcoal slurry. Even in the conscious patient, cough and gag reflexes may be so depressed as to necessitate special attention to protection against aspiration of gastric contents and orally administered materials. Convulsions should be treated with a short-acting barbiturate given intravenously and carefully titrated for the smallest effective dosage. Intensive support of respiration and cardiovascular-renal function is an essential feature of the treatment of severe intoxication from overdosage.

Do not use CNS stimulants.

DOSAGE AND ADMINISTRATION

Adults and children over 10: Usual dose is one 100 mg or 200 mg capsule t.i.d. as required. If necessary, up to 600 mg daily may be given.

HOW SUPPLIED

Benzonatate capsules, USP 100 mg are round, white soft gelatin capsules, imprinted in black ink “E,” packaged as follows:

NDC 58177-091-04 bottle of 100 capsules

NDC 58177-091-08 bottle of 500 capsules

NDC 58177-091-11 unit dose package of 100 capsules (10 capsules per blister card)

Benzonatate capsules, USP 200 mg are oval, white soft gelatin capsules, imprinted in black ink “E2,” packaged as follows:

NDC 58177-092-04 bottle of 100 capsules

Store at 25°C (77°F); excursions permitted to 15°-30°C (59°-86°F). [See USP Controlled Room Temperature.] Protect from light.

Dispense in a tight, light resistant container as defined in the USP.

Manufactured by
AccuCaps
Windsor, Ontario, Canada
for
ETHEX Corporation
St. Louis, MO 63044 USA

P5519-1 01/08